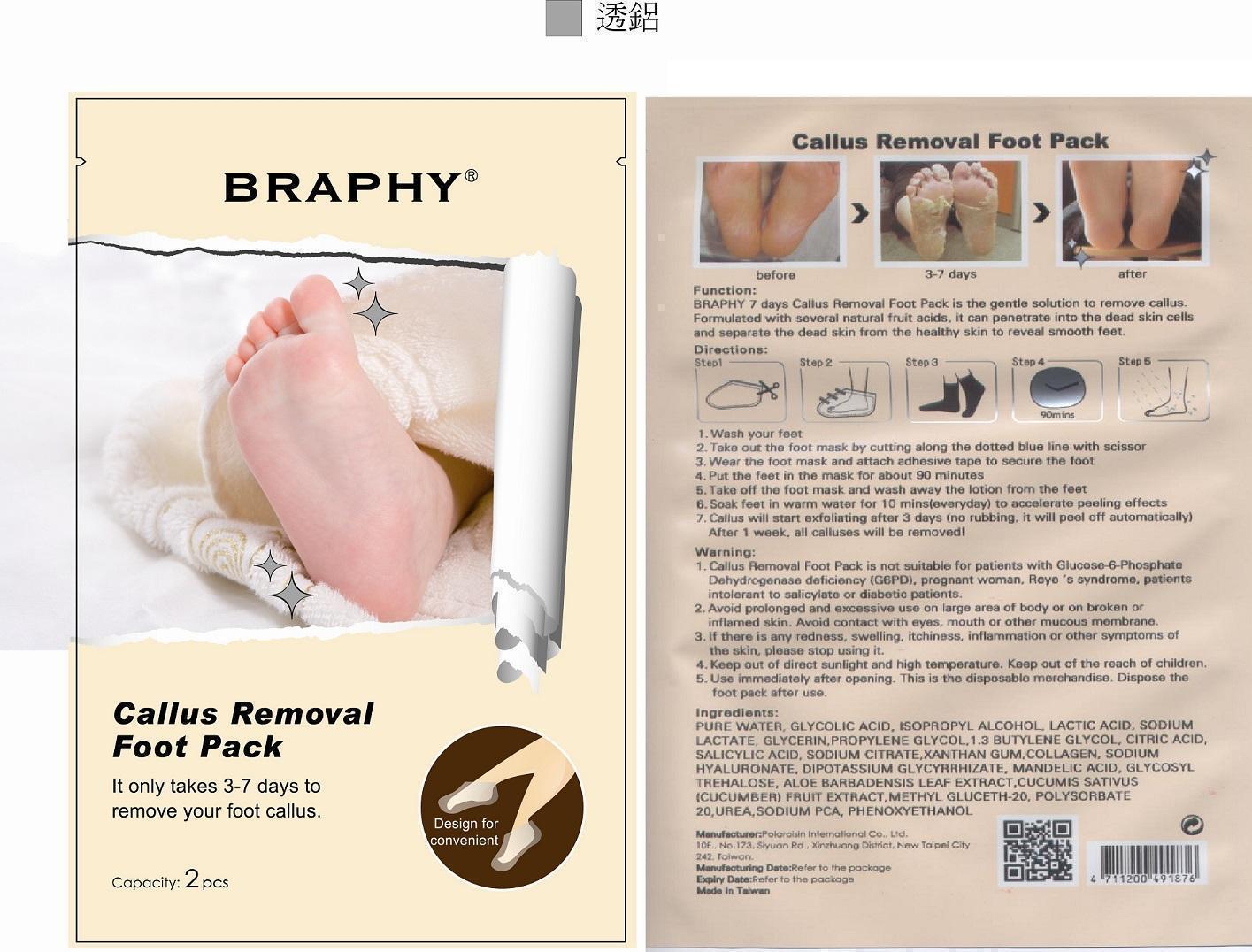 DRUG LABEL: Callus Removal Foot Pack
NDC: 69264-014 | Form: PATCH
Manufacturer: POLAROISIN INTERNATIONAL CO., LTD.
Category: otc | Type: HUMAN OTC DRUG LABEL
Date: 20141016

ACTIVE INGREDIENTS: SALICYLIC ACID 0.19 mg/1 1
INACTIVE INGREDIENTS: LACTIC ACID; WATER; GLYCOLIC ACID; ISOPROPYL ALCOHOL; SODIUM LACTATE; GLYCERIN; PROPYLENE GLYCOL; BUTYLENE GLYCOL; CITRIC ACID MONOHYDRATE; SODIUM CITRATE; XANTHAN GUM; COLLAGEN ALPHA-1(III) (HUMAN); HYALURONATE SODIUM; GLYCYRRHIZINATE DIPOTASSIUM; MANDELIC ACID; ALOE VERA LEAF; CUCUMBER; METHYL GLUCETH-20; POLYSORBATE 20; UREA; SODIUM PYRROLIDONE CARBOXYLATE; PHENOXYETHANOL; TREHALOSE

Callus Removal Foot Pack

ACTIVE INGREDIENT

Salicylic acid 0.19%

PURPOSE

Remove callus

Keep out of reach of children

Function

Braphy 7 days Callus removal foot pack is the gentle solution to remove callus. Formulated with several natural fruit acids, it can penetrate in to the dead skin cells and separate the dead skin from the healthy skin to reveal smooth feet

Warning

1. Callus Removal Foot Pack is not suitable for patients with Glucose -6-Phosphate Dehydrogenase deficiency (G6PD), pregnant woman, Reye's syndrome, patients intolerant to salicylate or diabetic patients.
2. Avoid prolonged and excessive use on large area of body or on broken or inflamed skin. Avoid contact with eyes, mouth or other mucous membrane.
3. If there is any redness, swelling, itchiness, inflammation or other symptoms of the skin, please stop using it.
4. keep out of direct sun light and high temperature.
5. Use immediately after opening .This is the disposable merchandise. Dispose the foot packs after use.

Directions

1. Wash your feet
2. Take out the foot mask by cutting along the dotted blue line with scissor
3. Wear the foot mask and attach adhesive tape to secure the foot
4. Put the feet in the mask for about 90 minutes
5. Take off the foot mask and wash away the lotion from the feet
6. Soak feet in warm water for10 mins(every day) to accelerate peeling effects
7. Callus will start exfoliating after 3 days (no rubbing, it will peel off automatically). After 1 week, all calluses will be removed!

Ingredients

PURE WATER, GLYCOLIC ACID, ISOPROPYL ALCOHOL, LACTIC ACID, SODIUM LACTATE, GLYCERIN, PROPYLENE GLYCOL,1.3 BUTYLENE GLYCOL, CITRIC ACID, SODIUM CITRATE, XANTHAN GUM,COLLAGEN, SODIUM HYALURONATE, DIPOTASSIUM GLYCYRRHIZATE,MANDELIC ACID, GLYCOSYL TREHALOSE, ALOE BARBADENSIS LEAF EXTRACT, CUCUMIS SATIVUS (CUCUMBER) FRUIT EXTRACT, METHYL GLUCETH-20, POLYSORBATE 20, UREA, SODIUM PCA, PHENOXY ETHANOL.